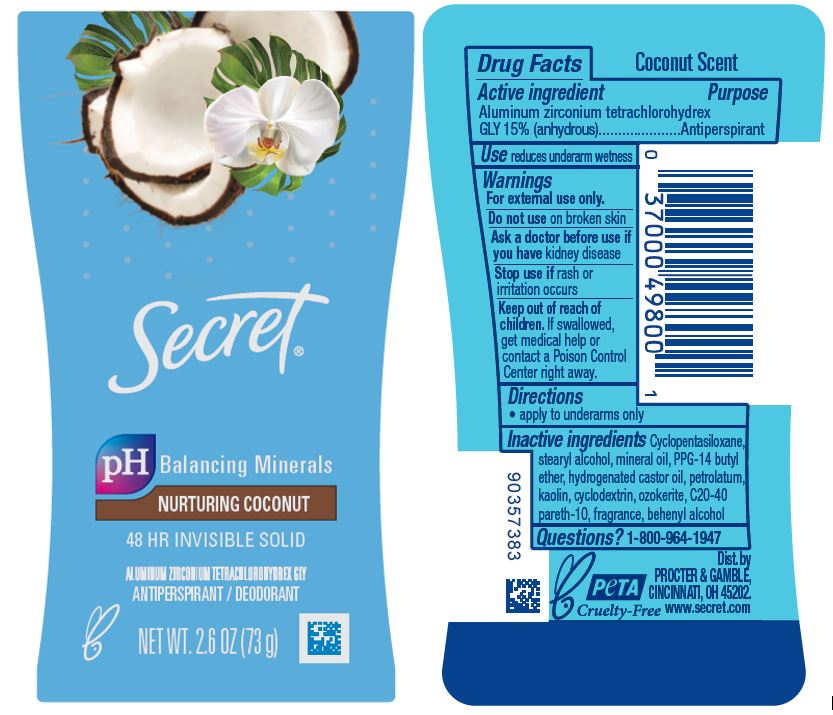 DRUG LABEL: Secret Nurturing Coconut Invisible
NDC: 69423-674 | Form: STICK
Manufacturer: The Procter & Gamble Manufacturing Company
Category: otc | Type: HUMAN OTC DRUG LABEL
Date: 20260106

ACTIVE INGREDIENTS: ALUMINUM ZIRCONIUM TETRACHLOROHYDREX GLY 15 g/100 g
INACTIVE INGREDIENTS: C20-40 PARETH-10; HYDROGENATED CASTOR OIL; CYCLOPENTASILOXANE; STEARYL ALCOHOL; PPG-14 BUTYL ETHER; PETROLATUM; KAOLIN; MINERAL OIL; BEHENYL ALCOHOL; CYCLODEXTRINS; CERESIN

Secret Nurturing Coconut 48 Hr Invisible Solid

Drug Facts

Active ingredient

Aluminum zirconium tetrachlorohydrex Gly 15% (anhydrous)

Purpose

Antiperspirant

Use

reduces underarm wetness

Warnings

For external use only.

Do not use on broken skin

Ask a doctor before use if you have kidney disease

Stop use if rash or irritation occurs

Keep out of reach of children. If swallowed, get medical help or contact a Poison Control Center right away.

Directions

- apply to underarms only

Inactive ingredients

Cyclopentasiloxane, stearyl alcohol, mineral oil, PPG-14 butyl ether, hydrogenated castor oil, petrolatum, kaolin, cyclodextrin, ozokerite, C20-40 pareth-10, fragrance, behenyl alcohol

Questions?

1-800-964-1947

Dist. by PROCTER & GAMBLE,
CINCINNATI, OH 45202.

PRINCIPAL DISPLAY PANEL - 73 g Canister Label

Secret

pH Balancing Minerals

NURTURING COCONUT

48 HR INVISIBLE SOLID

ALUMINUM ZIRCONIUM TETRACHLOROHYDREX GLY

ANTIPERSPIRANT / DEODORANT

NET WT. 2.6 OZ (73 g)